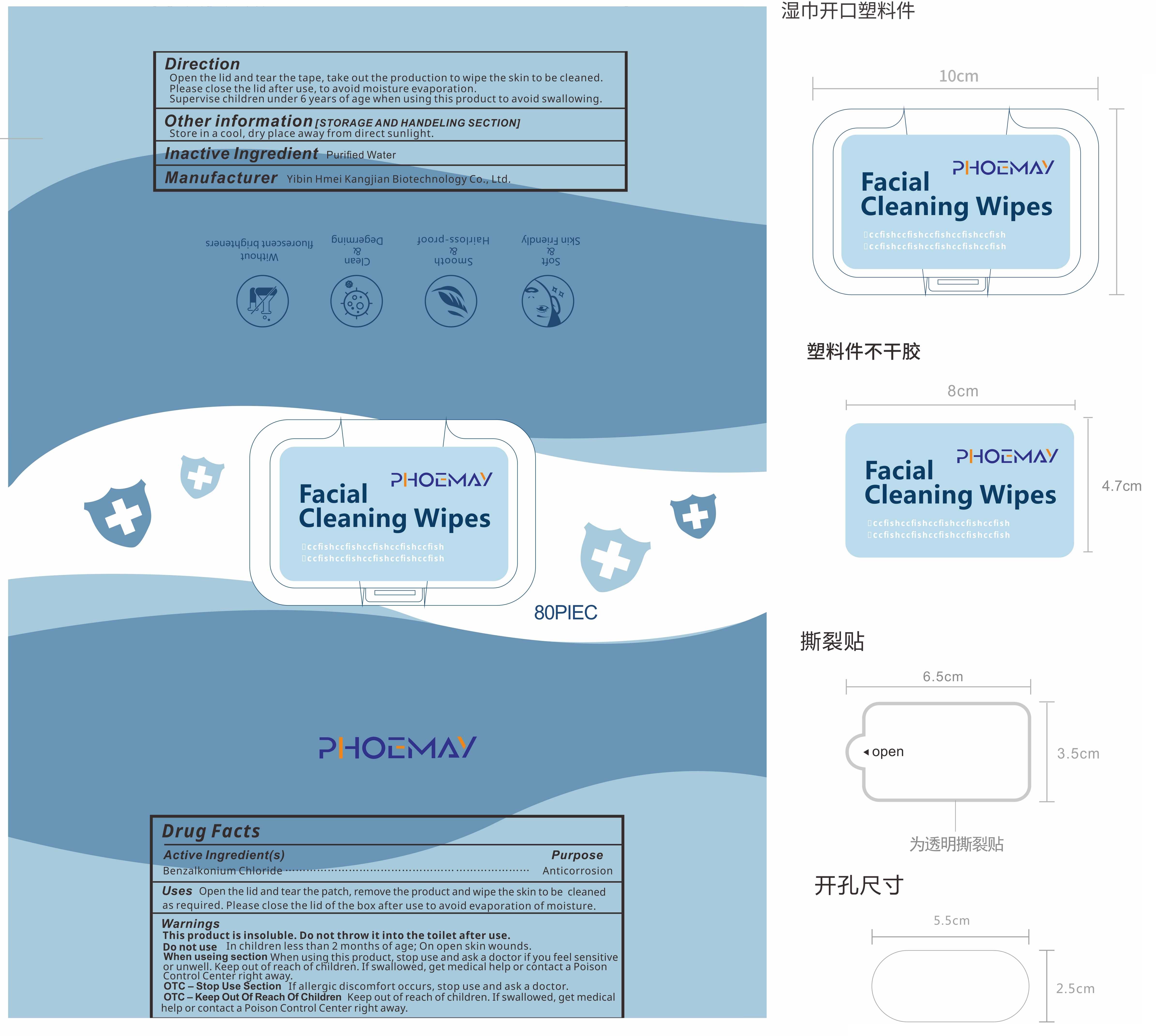 DRUG LABEL: Phoemay
NDC: 81392-001 | Form: CLOTH
Manufacturer: YIBIN HMEI KANGJIAN BIOTECHNOLOGY CO., LTD.
Category: otc | Type: HUMAN OTC DRUG LABEL
Date: 20210321

ACTIVE INGREDIENTS: BENZALKONIUM CHLORIDE 0.00008 g/100 1
INACTIVE INGREDIENTS: WATER

81392-001
Phoemay

Active Ingredient(s)

Benzalkonium Chloride 0.00008%

Purpose

Anticorrosion

Use

Open the lid and tear the patch, remove the product and wipe the skin to be cleaned as required.Please close the lid of the box after use to avoid evaporation of moisture.

Warnings

This product is insoluble.Do not throw it into the toilet after use.

Do not use

In children less than 2 months of age; On open skin wounds.

When using this product, stop use and ask a doctor if you feel sensitive or unwell.Keep out of reach of children.If swallowed, get medical help or contact a Poison Control Center right away.

STOP USE

If allergic discomfort occurs, stop use and ask a doctor.

Keep out of reach of children.If swallowed, get medical help or contact a Poison Control Center right away.

Directions

Open the lid and tear the tape, takeout the production to wipe the skin to be cleaned.
Please close the lid after use, to avoid moisture evaporation.
Supervise children under 6 years of age when using this product to avoid swallowing.

Other information

Store in a cool, dry place away from direct sunlight.

Inactive ingredients

Purified Water

Package Label - Principal Display Panel

81392-001-01 80P